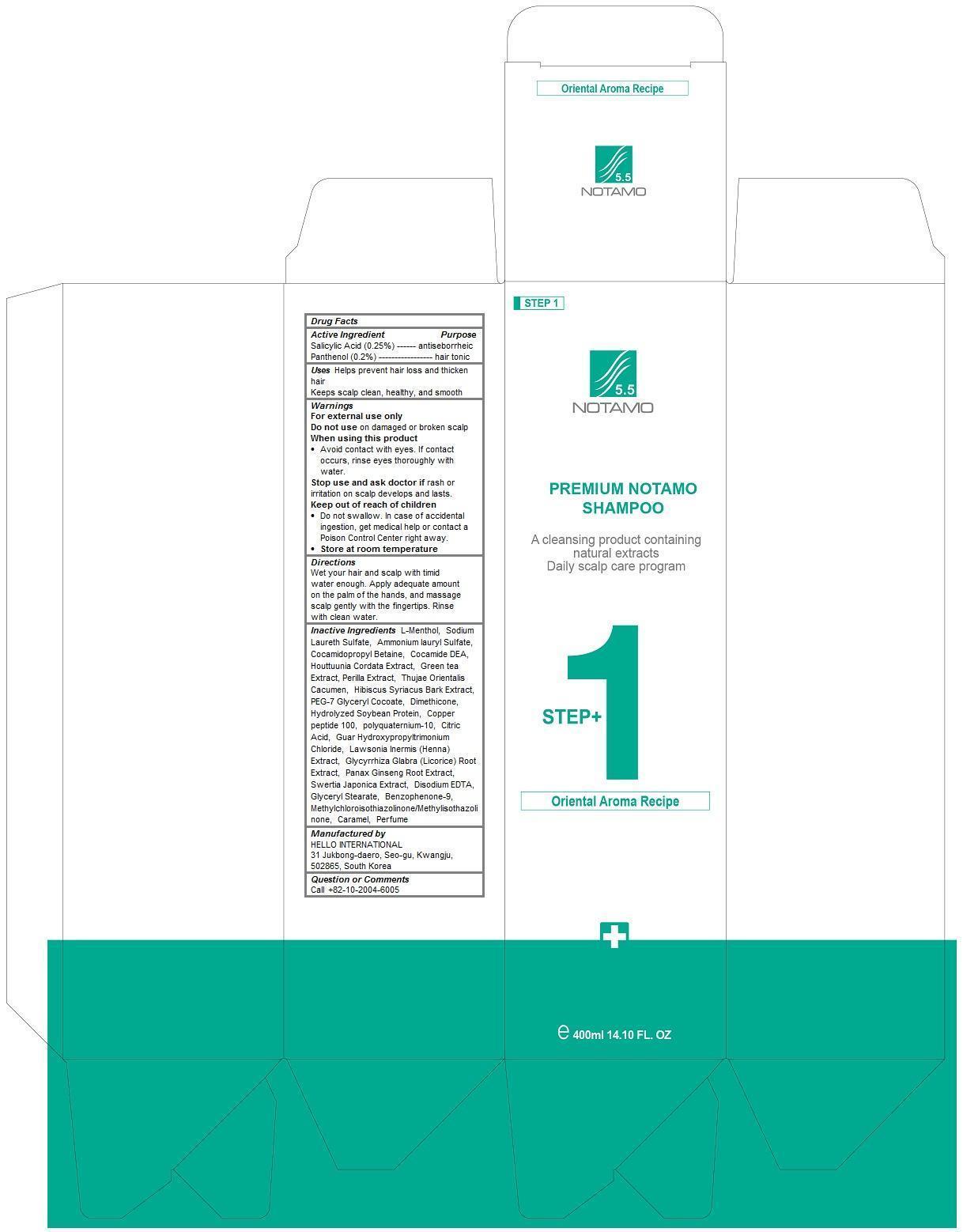 DRUG LABEL: Premium Notamo
NDC: 69709-101 | Form: SHAMPOO
Manufacturer: HELLO INTERNATIONAL
Category: homeopathic | Type: HUMAN OTC DRUG LABEL
Date: 20150404

ACTIVE INGREDIENTS: PANTHENOL 0.2 1/400 mL; SALICYLIC ACID 0.25 1/400 mL
INACTIVE INGREDIENTS: LEVOMENTHOL; Sodium Laureth Sulfate; Ammonium lauryl Sulfate; Cocamidopropyl Betaine; COCO DIETHANOLAMIDE; HOUTTUYNIA CORDATA FLOWERING TOP; GREEN TEA LEAF; HIBISCUS SYRIACUS BARK; PEG-7 GLYCERYL COCOATE; Dimethicone; POLYQUATERNIUM-10 (1000 MPA.S AT 2%); CITRIC ACID MONOHYDRATE; GUAR HYDROXYPROPYLTRIMONIUM CHLORIDE (1.7 SUBSTITUENTS PER SACCHARIDE); GLYCYRRHIZA GLABRA; ASIAN GINSENG; SWERTIA JAPONICA WHOLE FLOWERING; EDETATE DISODIUM; GLYCERYL MONOSTEARATE; BENZOPHENONE-9; METHYLCHLOROISOTHIAZOLINONE; CARAMEL

Premium Notamo Shampoo